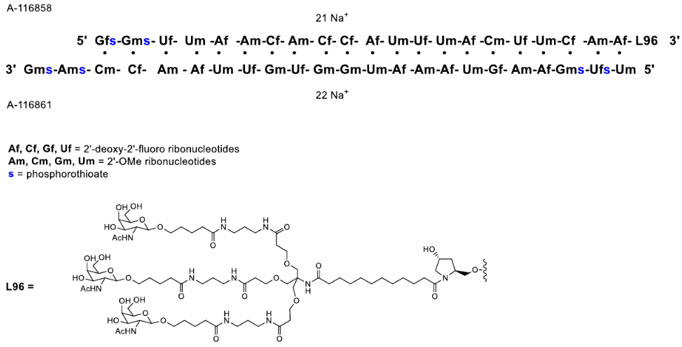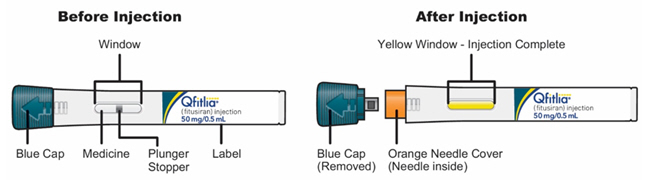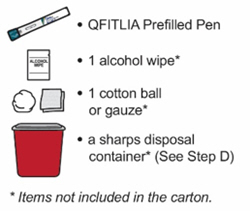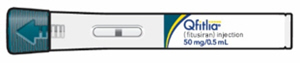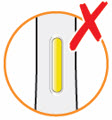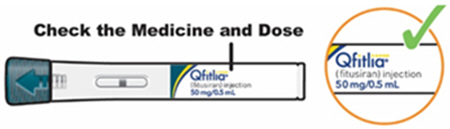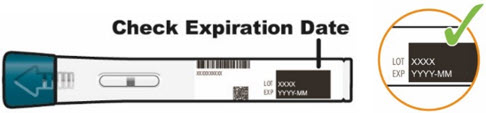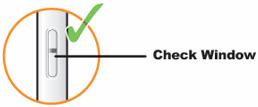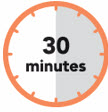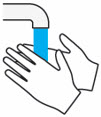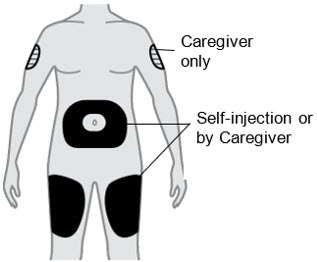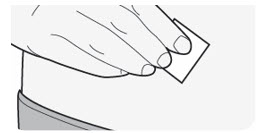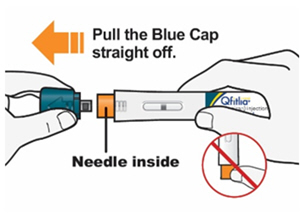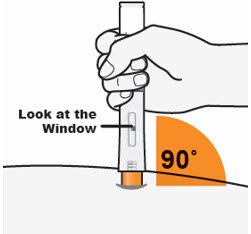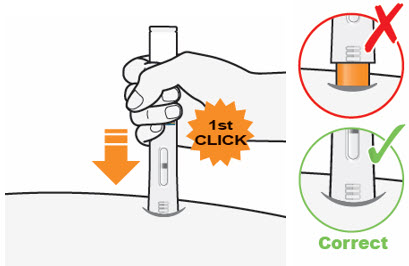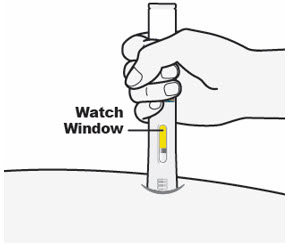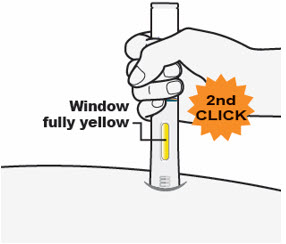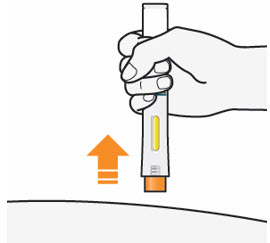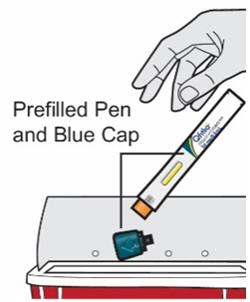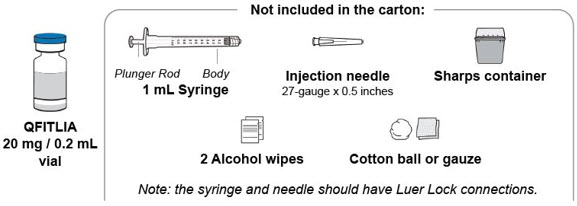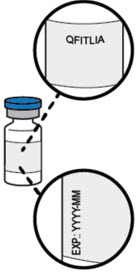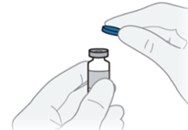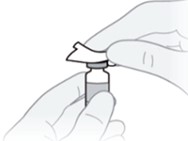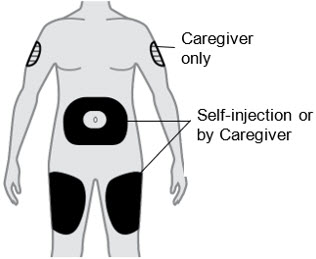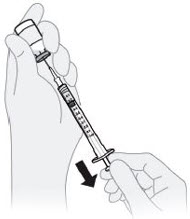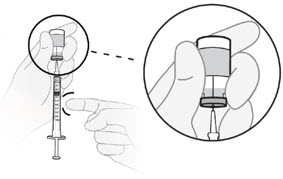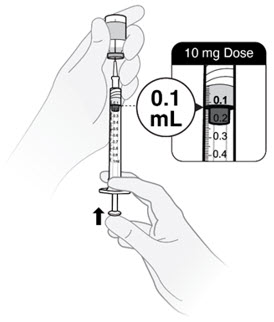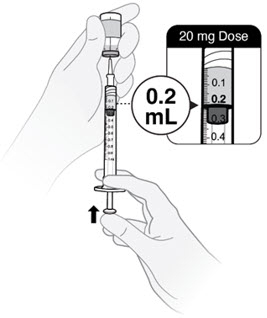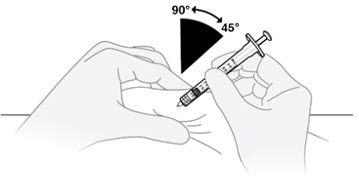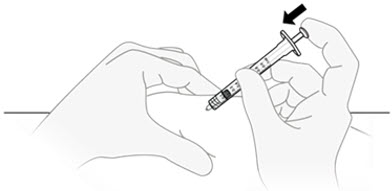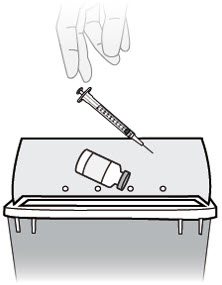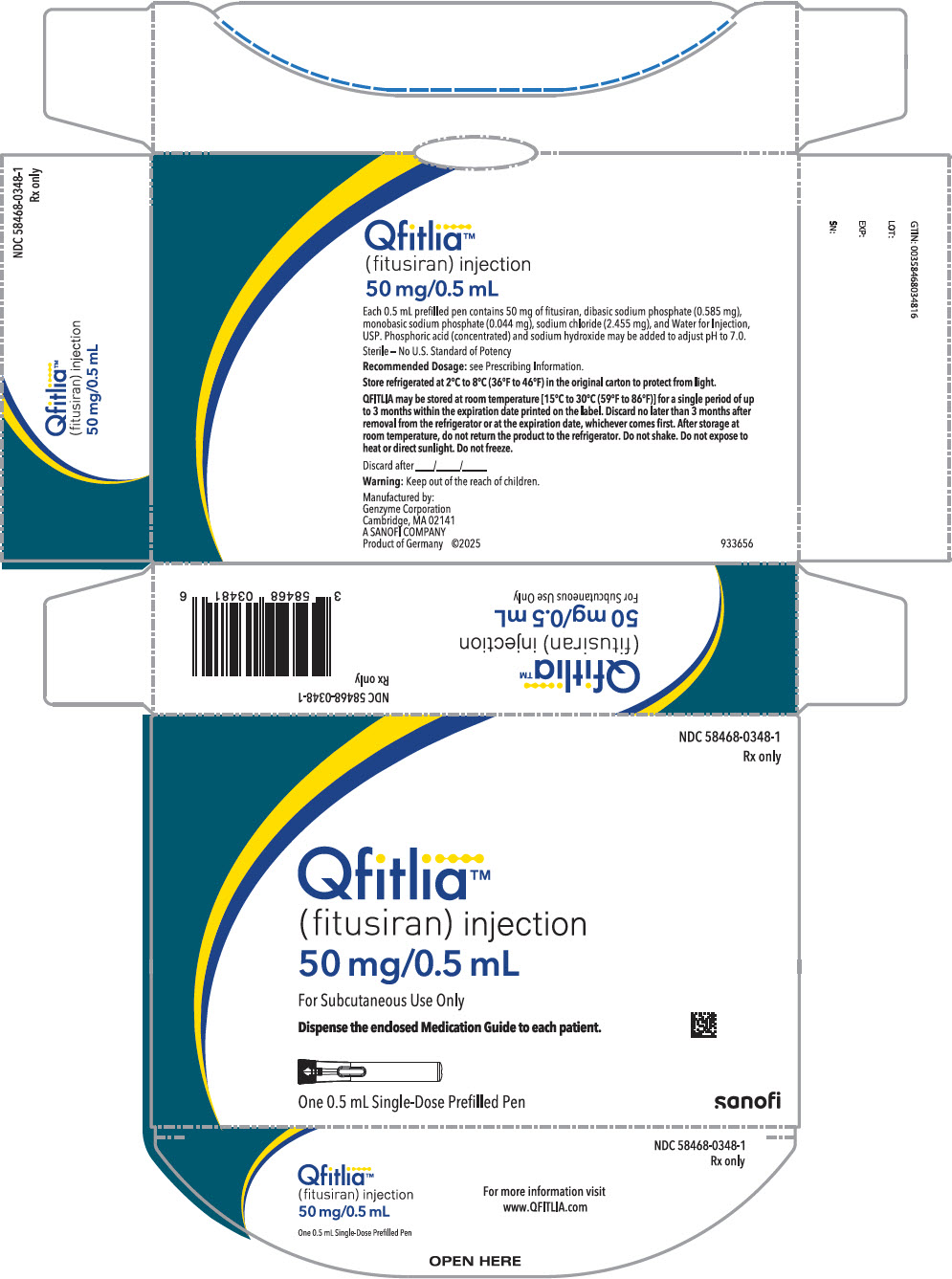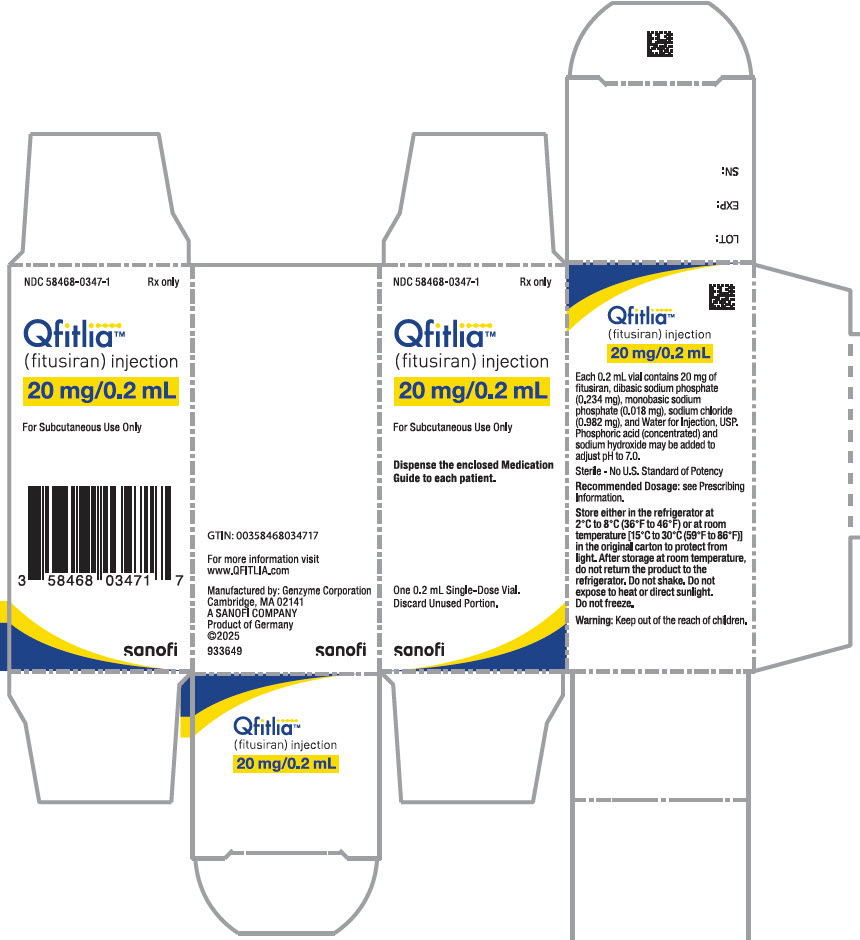 DRUG LABEL: Qfitlia
NDC: 58468-0348 | Form: INJECTION, SOLUTION
Manufacturer: Genzyme Corporation
Category: prescription | Type: HUMAN PRESCRIPTION DRUG LABEL
Date: 20250916

ACTIVE INGREDIENTS: FITUSIRAN 50 mg/0.5 mL
INACTIVE INGREDIENTS: SODIUM PHOSPHATE, DIBASIC, HEPTAHYDRATE 0.585 mg/0.5 mL; SODIUM PHOSPHATE, MONOBASIC, MONOHYDRATE 0.044 mg/0.5 mL; SODIUM CHLORIDE 2.455 mg/0.5 mL; WATER; PHOSPHORIC ACID; SODIUM HYDROXIDE

HIGHLIGHTS OF PRESCRIBING INFORMATION

These highlights do not include all the information needed to use QFITLIA® safely and effectively. See full prescribing information for QFITLIA.
QFITLIA (fitusiran) injection, for subcutaneous use
Initial U.S. Approval: 2025

WARNING: THROMBOTIC EVENTS AND ACUTE AND RECURRENT GALLBLADDER DISEASE

See full prescribing information for complete boxed warning.

Thrombotic Events

- Serious thrombotic events have occurred in QFITLIA-treated patients with risk factors including persistent antithrombin (AT) activity less than 15%, QFITLIA 80 mg once monthly dosing, an indwelling venous catheter, and the post-operative setting when bleed management guidelines were not followed.
- Interrupt QFITLIA in patients with a thrombotic event and manage as clinically indicated. (5.1)

Acute and Recurrent Gallbladder Disease

- Gallbladder disease has occurred in QFITLIA-treated patients, some requiring cholecystectomy or developing complications (e.g., pancreatitis).
- Monitor for signs and symptoms of gallbladder disease. Consider interruption or discontinuation of QFITLIA if gallbladder disease occurs.
- Consider alternative treatment for hemophilia if history of symptomatic gallbladder disease. (5.2)

1 INDICATIONS AND USAGE

QFITLIA is an antithrombin-directed small interfering ribonucleic acid indicated for routine prophylaxis to prevent or reduce the frequency of bleeding episodes in adult and pediatric patients aged 12 years and older with hemophilia A or B with or without factor VIII or IX inhibitors. (1)

2 DOSAGE AND ADMINISTRATION

- For subcutaneous use only.
- Starting dose: 50 mg once every 2 months (2.1).
- Monitor AT activity using an FDA-cleared test.
- Maintain AT activity between 15–35% by adjusting the dose and/or frequency of administration (2.2).

See Full Prescribing Information for important preparation and administration instructions (2.4).

3 DOSAGE FORMS AND STRENGTHS

Injection:

- 50 mg/0.5 mL (100 mg/mL) in a single-dose prefilled pen
- 20 mg/0.2 mL (100 mg/mL) in a single-dose vial (3)

4 CONTRAINDICATIONS

- None (4)

5 WARNINGS AND PRECAUTIONS

- Hepatotoxicity: Obtain liver tests at baseline and then monthly for at least 6 months after initiating QFITLIA and after dose increases, and periodically thereafter. Liver test elevations may require QFITLIA interruption or discontinuation (5.3).

6 ADVERSE REACTIONS

Common adverse reactions (incidence >10%) are viral infection, nasopharyngitis, and bacterial infection (6.1).

To report SUSPECTED ADVERSE REACTIONS, contact Genzyme Corporation 1-800-745-4447 or FDA at 1-800-FDA-1088 or www.fda.gov/medwatch.

8 USE IN SPECIFIC POPULATIONS

Avoid use in patients with established hepatic impairment (Child-Pugh Class A, B and C) (8.6).

To report SUSPECTED ADVERSE REACTIONS, contact Genzyme Corporation 1-800-745-4447 or FDA at 1-800-FDA-1088 or www.fda.gov/medwatch.

FULL PRESCRIBING INFORMATION

WARNING: THROMBOTIC EVENTS AND ACUTE AND RECURRENT GALLBLADDER DISEASE

Thrombotic Events

Serious thrombotic events have occurred in QFITLIA-treated patients with risk factors for thromboembolism including persistent antithrombin (AT) activity less than 15%, use of QFITLIA 80 mg once monthly, presence of indwelling venous catheters, and in the post-operative setting when bleed management guidelines were not followed.

Monitor AT activity using an FDA-cleared test and target AT activity 15–35% to reduce the risk of thrombosis. Monitor patients for signs and symptoms of thrombotic events. Interrupt QFITLIA in patients with a thrombotic event and manage as clinically indicated. (5.1)

Acute and Recurrent Gallbladder Disease

Acute and recurrent gallbladder disease, including cholelithiasis and cholecystitis have occurred in QFITLIA-treated patients, some of whom required cholecystectomy or had complications (e.g., pancreatitis) related to gallbladder disease. Monitor patients for signs and symptoms of acute and recurrent gallbladder disease.

Consider interruption or discontinuation of QFITLIA if gallbladder disease occurs. Consider alternative treatment for hemophilia in patients with a history of symptomatic gallbladder disease. (5.2)

1 INDICATIONS AND USAGE

QFITLIA is indicated for routine prophylaxis to prevent or reduce the frequency of bleeding episodes in adult and pediatric patients aged 12 years and older with hemophilia A or B with or without factor VIII or IX inhibitors.

2 DOSAGE AND ADMINISTRATION

2.1 Recommended Dosage

For subcutaneous use only.

Use of QFITLIA is recommended under the supervision of a healthcare professional experienced in the treatment of hemophilia or bleeding disorders.

Measure AT activity prior to initiation of QFITLIA. Do not initiate QFITLIA dosing if AT activity is <60%.

Monitor AT activity using an FDA-cleared test. Information on FDA-cleared tests for AT activity is available at http://www.fda.gov/CompanionDiagnostics.

After QFITLIA is initiated, patients may continue their prior clotting factor concentrates (CFC) or bypassing agent (BPA) prophylaxis for the first 7 days of treatment. Discontinue CFC or BPA prophylaxis no later than 7 days after the initial dose of QFITLIA.

The starting dose of QFITLIA is 50 mg once subcutaneously every two months. Adjust the dose and/or dosing interval, if needed, to maintain AT activity between 15–35% [see Boxed Warning, Dosage and Administration (2.2) and Warnings and Precautions (5.1)].

2.2 Dosage Modification

Measure AT activity using an FDA-cleared test at Weeks 4 (Month 1), 12 (Month 3), 20 (Month 5) and 24 (Month 6) following the starting dose and after any dose modification.

- If any AT activity is <15%, a dose reduction is required. The lower dose should be initiated 3 months after the prior dose. AT measurements should be restarted after a dose reduction.
- If AT activity is >35% after 6 months, or if the patient has not achieved satisfactory bleed control, dose escalation should be considered. AT measurements should be restarted after a dose escalation.

Refer to Table 1 below for modified dosage based on AT activity levels.

Table 1: Dose Modification Based on Antithrombin Activity Levels
Last Dosage Administered | Antithrombin Activity Level | Dose Modification
50 mg every 2 months | Less than 15% | 20 mg every 2 months
50 mg every 2 months | 15% to 35% | Continue current dosage
50 mg every 2 months | Greater than 35% after 6 months | 50 mg every month
20 mg every 2 months | Less than 15% | 10 mg every 2 months
20 mg every 2 months | 15% to 35% | Continue current dosage
20 mg every 2 months | Greater than 35% after 6 months | 20 mg every month
10 mg every 2 months | Less than 15% | Discontinue QFITLIA
10 mg every 2 months | 15% to 35% | Continue current dosage
10 mg every 2 months | Greater than 35% after 6 months | 10 mg every month

Once the patient's target dose is identified based on AT activity 15–35%, measure AT activity annually. Additional AT measurements can be considered if bleeding control is not adequate.

After cessation of QFITLIA dosing, routine AT monitoring is not needed unless the patient is bleeding and treatment with CFC/BPA is required. Based on data from the clinical studies, a majority of patients have AT activity >60% by 6 months after the last QFITLIA dose, after which standard doses of CFC/BPA may be used.

Missed dose

If a dose of QFITLIA is missed, administer as soon as possible; thereafter, resume the patient's usual dosing schedule of either once every month or once every two months, as applicable, from the last dose.

2.3 Bleed Management

Breakthrough Bleed Management

If breakthrough bleeding requiring on-demand treatment with CFC or BPA occurs during the first 7 days after QFITLIA initiation, manage the bleed using the patient's prior dosing regimen of CFC or BPA.

If breakthrough bleeding occurs after 7 days from the first QFITLIA dose, bleeds should be managed with a reduced dose and frequency of CFC/BPA to minimize the risk of thrombotic events. Initially, the weight-based dose of a CFC/BPA should be reduced, and the dosing interval doubled compared to the standard dose. This reduced dosing is shown in Table 2. If adequate hemostatic control is not achieved, higher doses may be used based on clinical judgement. Combination use of antifibrinolytics with CFC or BPA has not been studied.

Table 2: Breakthrough Bleed Management While Treated with QFITLIA
 | Factor VIII | Factor IX (SHL) | Factor IX (EHL) | aPCC | rFVIIa
Recommended dose | 10 IU/kg (maximum: 20 IU/kg) [Use clinical judgement for situations requiring higher doses, more frequent administration, or multiple repeat doses. Use standard of care for adjunctive management of bleeding episodes and thrombotic events.] | 20 IU/kg (maximum: 30 IU/kg) | 20 IU/kg (maximum: 30 IU/kg) | 30 U/kg (maximum: 50 U/kg) | ≤45 μg/kg
Repeat dosing | Should not repeat in <24 hours | Should not repeat in <24 hours | Should not repeat in <5–7 days | Should not repeat in <24 hours | Should not repeat in <2 hours
aPCC = activated prothrombin complex concentrate, EHL = extended half-life, rFVIIa = activated recombinant FVII, SHL = standard half-life.

Use of QFITLIA During Surgical Interventions

In clinical studies, patients with hemophilia A or B with or without inhibitors have undergone both major (N=60) and minor (N=71) surgical procedures without discontinuing QFITLIA prophylaxis. Utilize bleed management guidelines during the perioperative period for hemostatic management.

2.4 Preparation and Administration Instructions

QFITLIA is intended for use under the guidance of a healthcare provider. Provide proper training to patients and/or caregivers on the preparation and administration of QFITLIA prior to use, according to the Instructions for Use (IFU). A patient may self-inject QFITLIA or the patient's caregiver may administer QFITLIA. In pediatric patients 12 to 17 years of age, it is recommended that QFITLIA be administered by or under the supervision of an adult.

QFITLIA for subcutaneous administration is a clear, colorless to pale yellow solution. Do not use if the solution is discolored or cloudy, or if it contains visible flakes or particles. Do not use QFITLIA if it has been dropped or damaged.

If QFITLIA is stored at room temperature, it is ready for use. If QFITLIA is stored in the refrigerator, remove from the refrigerator and allow QFITLIA to reach room temperature, for at least 30 minutes.

Administer QFITLIA by subcutaneous injection in the thigh or abdomen region, except for the 2 inches (5 cm) around the navel. A caregiver can also inject QFITLIA in the outer area of the patient's upper arm. QFITLIA should not be injected into skin that is tender, damaged, bruised, or scarred. Do not inject into a vein.

To inject 10 mg or 20 mg of QFITLIA from the single-dose vial, it is recommended to use a sterile 1 mL Luer Lock syringe (polypropylene or polycarbonate), and a sterile 27 gauge ½ inch (13 mm) Luer Lock needle to withdraw and inject QFITLIA solution subcutaneously (see the Instructions for Use).

Discard unused product remaining in the prefilled pen or vial.

3 DOSAGE FORMS AND STRENGTHS

QFITLIA is a clear, colorless to pale yellow solution in a single-dose:

- Injection: 50 mg/0.5 mL prefilled pen
- Injection: 20 mg/0.2 mL vial

4 CONTRAINDICATIONS

None.

5 WARNINGS AND PRECAUTIONS

5.1 Thrombotic Events

Serious thrombotic events have been reported in QFITLIA-treated patients. Thrombotic events were reported in 2.6% of patients receiving the 80 mg once monthly dose (2.3 events per 100 person-years), including a fatal event of cerebral venous sinus thrombosis. The 80 mg once monthly dose is not approved or recommended for use. Thrombotic events were reported in 1.4% of patients receiving QFITLIA prophylaxis using the antithrombin-based dose regimen (AT-DR) that targeted AT activity 15-35% (0.8 events per 100 person-years). Participants with established thrombophilia or a history of thrombosis were generally excluded from studies with QFITLIA.

The risk of thrombosis is greater in patients with persistent AT activity <15%, with comorbidities that predispose to thrombosis, when bleed management guidelines are not followed in the post-operative setting, when there is an indwelling venous catheter, and with use of the 80 mg once monthly (non-AT-based) dose. Treatment of breakthrough bleeding episodes with CFC or BPA at a dose greater or more frequent than recommended may also increase thrombotic risk [see Dosage and Administration (2.3)]. The decision to utilize higher dosing regimens of CFC or BPA in the setting of inadequate hemostasis requires an assessment of the benefits and risks and close clinical monitoring.

Monitor AT activity using an FDA-cleared test and target AT activity 15–35% to reduce the risk of thrombosis [see Dosage and Administration (2.1, 2.2) and Warnings and Precautions (5.1)]. Monitor patients for signs and symptoms of thrombotic events. Interrupt QFITLIA prophylaxis in patients with a thrombotic event and manage as clinically indicated.

Inform patients treated with QFITLIA to monitor for and report signs and symptoms of thrombotic events. Consider the benefits and risks of resuming QFITLIA prophylaxis following resolution of the thrombotic event.

5.2 Acute and Recurrent Gallbladder Disease

Treatment with QFITLIA is associated with an increased occurrence of acute and recurrent gallbladder disease including cholelithiasis and cholecystitis. QFITLIA at a fixed dose (including 80 mg once monthly) is not approved or recommended for use. In the 270 patients in the QFITLIA clinical studies who received the fixed dose (non-AT-based dose) once monthly regimen, 17% experienced gallbladder events and 4% (11 patients) underwent cholecystectomy.

In 286 patients who received the AT-DR, 3.8% experienced gallbladder events and 0.3% (1 patient) underwent cholecystectomy.

All but one of the patients who underwent cholecystectomy resumed QFITLIA after surgery. One patient who started on fixed dosing experienced cholangitis and pancreatitis caused by gallstone disease more than a year after cholecystectomy while receiving AT-DR.

Patients diagnosed with acute or recurrent gallbladder disease most commonly presented with epigastric pain, generalized abdominal pain, indigestion, nausea and/or vomiting. If gallbladder disease is suspected, appropriate imaging and clinical follow-up are indicated.

Consider alternative treatment for hemophilia in patients with a history of symptomatic gallbladder disease. Consider interruption or discontinuation of QFITLIA if gallbladder disease occurs.

5.3 Hepatotoxicity

In the two randomized studies testing QFITLIA 80 mg once monthly, serum alanine transaminase (ALT) and aspartate transaminase (AST) elevations above 3 times the upper limit of normal (ULN) occurred in 32% of patients with hemophilia with inhibitors and 18% of patients with hemophilia without inhibitors compared to no events of AST or ALT elevation greater than 3× ULN in the control groups. There was one case of moderate hepatic injury (ALT elevation >300 U/L and total serum bilirubin >3 mg/dL) attributable to QFITLIA use. This patient had elevation of liver tests after a single 80 mg dose that continued to rise with repeated dosing of QFITLIA 80 mg once monthly. This patient's liver tests recovered with drug discontinuation. QFITLIA 80 mg once monthly is not approved or recommended for use.

On the AT-DR, 3.4% of patients treated with QFITLIA had at least one ALT value greater than 3× ULN with a median onset of 89 days after initial dosing (range 15 to 768 days).

Avoid use of QFITLIA in patients with hepatic impairment (Child-Pugh Class A, B and C).

Obtain baseline liver tests including AST, ALT, and total bilirubin prior to initiating QFITLIA, monthly for at least the first 6 months of QFITLIA use, and monthly for at least 6 months after a dose increase, and periodically thereafter as clinically indicated.

If new or worsening liver test abnormalities occur, perform appropriate diagnostic evaluations, initiate medical management as appropriate and monitor laboratory parameters until they return to baseline. If ALT or AST elevations greater than 5× ULN occur, interrupt QFITLIA treatment. Consider the benefits and risks of resuming QFITLIA prophylaxis following resolution of transaminase elevations. If you decide to restart QFITLIA, wait until liver tests have returned to baseline. If QFITLIA is restarted and ALT or AST elevations greater than 5× ULN reoccur or the patient experiences jaundice (total bilirubin ≥2.5 mg/dL) thought to be from hepatotoxicity with other causes of liver test elevation ruled out, permanently discontinue QFITLIA.

6 ADVERSE REACTIONS

The following clinically significant adverse reactions are described elsewhere in the labeling:

- Thrombotic Events [see Boxed Warning and Warnings and Precautions (5.1)]
- Acute and Recurrent Gallbladder Disease [see Boxed Warning and Warnings and Precautions (5.2)]
- Hepatotoxicity [see Warnings and Precautions (5.3)]

6.1 Clinical Trials Experience

Because clinical trials are conducted under widely varying conditions, adverse reaction rates observed in the clinical trials of a drug cannot be directly compared to rates in the clinical trials of another drug and may not reflect the rates observed in practice.

The pooled safety population described in the WARNINGS AND PRECAUTIONS reflect exposure to QFITLIA as fixed doses and AT-DR (N=335).

The safety of the QFITLIA AT-DR was assessed in 286 adult and pediatric male patients with hemophilia A or B with or without inhibitors [see Clinical Studies (14)].

Among patients who received the AT-DR, 93% were exposed for 6 months or longer and 83% were exposed for 12 months or longer. The median duration of exposure across the studies was 674 days (with a maximum of 896 days).

Serious adverse reactions occurred in 4/286 (1.4%) patients who received the AT-DR, two of whom had serious adverse reactions of cholecystitis.

Permanent discontinuation of QFITLIA due to an adverse reaction occurred in 4/286 (1.4%) patients receiving the AT-DR and included liver injury, post-operative deep vein thrombosis, cerebral infarction and pruritus.

Dosage interruptions of QFITLIA due to an adverse reaction occurred in 2/286 (0.7%) patients receiving the AT-DR and included increased serum transaminases.

The most common adverse reactions (≥10%) reported in patients treated with the AT-DR were viral infection, nasopharyngitis, and bacterial infection.

Table 3: Adverse Reactions Reported in ≥5% of Patients from Pooled Clinical Studies with QFITLIA AT-DR
Adverse Reaction | Number of Patients (%) N=286
Viral infection [Includes similar terms.] | 29
Nasopharyngitis | 26
Bacterial infection | 11
Hepatic Injury [Hepatic injury includes: alanine aminotransferase increased, aspartate aminotransferase increased, liver injury.] | 8
Arthralgia | 8
Prothrombin fragment 1.2 increased | 7
Injection site reaction [injection site reactions: includes injection site bruising, injection site erythema, injection site pain, injection site hematoma, injection site atrophy, injection site hemorrhage, injection site discomfort, injection site swelling, injection site discoloration, injection site pruritus, injection site induration, injection site nodule, injection site mass, injection site vesicles, injection site deformation, injection site rash, injection site joint pain and application site erythema.] | 6
Headache | 5
Cough | 5

Clinically relevant adverse reactions in less than 5% of patients include:

- Dyspepsia
- Abdominal pain

7 DRUG INTERACTIONS

7.1 Hypercoagulability with Concomitant Use of CFC or BPA

QFITLIA prophylaxis leads to increased thrombin generation with additive increase in peak thrombin when used concomitantly with CFC or BPA [see Boxed Warning, Dosage and Administration (2.3) and Warnings and Precautions (5.1)].

8 USE IN SPECIFIC POPULATIONS

8.1 Pregnancy

Risk Summary

There are no available data on QFITLIA use in pregnant women to evaluate for a drug-associated risk of major birth defects, miscarriage, or other adverse maternal or fetal outcomes. Reproduction studies in pregnant animals have not been conducted with fitusiran. It is not known whether QFITLIA can cause fetal harm when administered to a pregnant woman or can affect reproduction capacity. QFITLIA should be used during pregnancy only if the potential benefit justifies the potential risks, including those to the fetus.

The estimated background risk of major birth defects and miscarriage for the indicated population is unknown. All pregnancies have a background risk of birth defect, loss, or other adverse outcomes. In the U.S. general population, the estimated background risk of major birth defects and miscarriage in clinically recognized pregnancies is 2–4% and 15–20%, respectively.

8.2 Lactation

Risk Summary

There are no data on the presence of fitusiran or its metabolite in human milk, the effects on the breastfed child, or the effects on milk production. It is not known whether QFITLIA is safe for use during breastfeeding. The developmental and health benefits of breastfeeding should be considered along with the mother's clinical need for QFITLIA and any potential adverse effects on the breastfed infant from QFITLIA or from the underlying maternal condition.

8.3 Females and Males of Reproductive Potential

Contraception

Females

Use of QFITLIA in women using hormonal contraceptives may increase the risk of thrombotic events. Estrogen based hormonal contraceptives are an established risk factor for thrombosis in women with inherited AT deficiency. Advise patients using hormonal contraceptives to use an alternative non-hormonal contraception prior to starting treatment with and while receiving QFITLIA.

8.4 Pediatric Use

The safety and effectiveness of QFITLIA for the treatment of hemophilia A or B with or without factor VIII or IX inhibitors have been established in pediatric patients aged 12 years and older. Use of QFITLIA in pediatric patients with hemophilia A and B is supported by evidence from adequate and well-controlled studies in adult and pediatric patients [see Adverse Reactions (6.1) and Clinical Studies (14)]. A total of 60 pediatric patients ages 12 to 17 were treated with QFITLIA in the clinical studies.

The safety and effectiveness of QFITLIA have not been established in pediatric patients below 12 years of age.

8.5 Geriatric Use

There were 3 patients with hemophilia 65 years of age and older in the clinical studies on QFITLIA. Clinical studies of QFITLIA did not include sufficient numbers of subjects aged 65 and over to determine whether they respond differently from younger subjects.

8.6 Hepatic Impairment

Serum transaminase elevations have been observed in the clinical studies [see Warnings and Precautions (5.3)]. Avoid use of QFITLIA in patients with established hepatic impairment (Child-Pugh Class A, B and C).

11 DESCRIPTION

QFITLIA injection contains fitusiran, an antithrombin-directed double-stranded small interfering ribonucleic acid (siRNA), which is covalently linked to a ligand containing a triantennary N-acetylgalactosamine (GalNAc) moiety. The molecular formula of fitusiran sodium is C520H636F21N175Na43O309P43S6 and the molecular weight is 17,193 Da. Fitusiran drug substance is a white to pale yellow powder and freely soluble in water and phosphate buffered saline. The pH of a 1% aqueous solution of fitusiran drug substance in 50 mM KCl is 5.4 (4.4–7.3). It has the following structural formula:

QFITLIA is supplied as a sterile, preservative-free, clear, colorless to pale yellow solution for subcutaneous administration.

Each 50 mg single-dose prefilled pen delivers 50 mg fitusiran (equivalent to 53.0 mg fitusiran sodium) in 0.5 mL, and also contains dibasic sodium phosphate (0.585 mg), monobasic sodium phosphate (0.044 mg), sodium chloride (2.455 mg), and Water for Injection, USP. Phosphoric acid (concentrated) and sodium hydroxide may be added to adjust to pH 7.0.

Each 20 mg single-dose vial delivers 20 mg fitusiran (equivalent to 21.2 mg fitusiran sodium) in 0.2 mL, and also contains dibasic sodium phosphate (0.234 mg), monobasic sodium phosphate (0.018 mg), sodium chloride (0.982 mg), and Water for Injection, USP. Phosphoric acid (concentrated) and sodium hydroxide may be added to adjust to pH 7.0.

12 CLINICAL PHARMACOLOGY

12.1 Mechanism of Action

QFITLIA is a double-stranded siRNA that causes degradation of AT messenger RNA (mRNA) through RNA interference, reducing plasma AT levels.

12.2 Pharmacodynamics

In clinical studies with QFITLIA in hemophilia patients, the primary pharmacodynamic (PD) measure was plasma AT activity. Lower AT activity levels were associated with lower annualized bleeding rates (ABR); however, persistent AT activity <15% is a risk factor for thrombotic events.

In Study LTE15174, the mean (SD) AT activity on the AT-DR was 24% (4.64).

Simulations to estimate time for AT activity to reach steady state found that regardless of the dose regimen, more than 99% of participants reached steady state AT levels (defined as <10% variability among consecutive measures) within 23 weeks following initiation of QFITLIA dosing or following dose escalation or de-escalation. The duration of persistent AT activity <60% (non-negligible impact of QFITLIA on coagulation) following QFITLIA treatment discontinuation was estimated to be approximately 6 months, after which standard doses of CFC/BPA may be administered. In patients with AT activity <15%, the time required prior to initiation of a lower dose was estimated to be 12 weeks to maximize the AT activity recovery to the target range of 15% to 35%. Extent of AT reduction with QFITLIA did not differ between patients with hemophilia A or B, with or without inhibitors.

12.3 Pharmacokinetics

The pharmacokinetic (PK) properties of fitusiran were evaluated following administration of QFITLIA in patients with hemophilia A or B, with or without inhibitors as summarized in Table 4. QFITLIA PD is driven by liver PK rather than plasma PK. The QFITLIA dosing strategy is based on maintaining plasma AT activity levels between 15–35% with 10, 20 or 50 mg dosing every month or every two months.

Table 4: Pharmacokinetic Parameters of QFITLIA
PK Parameters [Unless otherwise indicated, the PK parameters in this table are from Study LTE15174. All PK parameters are estimated using non-compartmental analysis and are presented as Mean (SD) [CV%], except for tmax which is presented as median (range)] | QFITLIA 20 mg | QFITLIA 50 mg
General Information
Steady State Exposure:
Cmax (ng/mL) | 34.4 (10.1) [29%] | 84.1 (58.7) [70%]
AUC (ng∙h/mL) | 491 (83.8) [17%] | 1290 (377) [29%]
Dose Proportionality | QFITLIA exhibited a dose proportional increase in plasma exposure after SC administration.
Accumulation [Study TDR14767 (ALN-AT3SC-001)] | No accumulation of QFITLIA was observed following multiple once monthly dosing.
Absorption
tmax (h) | 2.88 (0.5 – 4.33) | 3.78 (0.42 – 11.9)
Distribution [QFITLIA distributes primarily to the liver after subcutaneous injection.]
Vss/F | 431 (135) [31%] | 570 (713) [125%]
Protein Binding [In vitro data] | 96.6% at clinically relevant exposure (0.5 microgram/ml)
Elimination
t1/2 (h) | 5.57 (2.36) [42%] | 7.98 (4.74) [59%]
CL/F | 41.9 (8.39) [20%] | 50.8 (71.1) [140%]
Metabolism
Primary Pathway | QFITLIA is metabolized by endo- and exo-nucleases to oligonucleotides of varying lengths, which are further metabolized to oligonucleotides of even shorter lengths. QFITLIA is not a substrate for CYP450 or transporters.
Main Metabolite | AS(N-1)3'
Excretion
Primary Pathway | Not evaluated | 14.6% (mean) of the administered 50 mg dose of QFITLIA is recovered unchanged in 0–24 hour urine
AUC = area under the plasma concentration-time curve extrapolated to infinity; CL/F = apparent clearance; Cmax = maximum plasma concentration; CV = coefficient of variation; PK = pharmacokinetic(s); SD = standard deviation; t1/2 = terminal elimination half-life; tmax = time to maximum concentration; Vss/F = apparent volume of distribution

Specific Populations

QFITLIA has only been studied in male patients. The pharmacokinetics of fitusiran is not influenced by race. QFITLIA has not been studied in children <12 years old.

No clinical study to evaluate the effect of hepatic impairment or renal impairment on the pharmacokinetics of QFITLIA was conducted. In the pivotal studies, 12 patients had mild renal impairment (eGFR ≥60 to <90 mL/min/1.73 m^2) and 1 patient had moderate renal impairment (eGFR 30 mL/min/1.73 m^2 to <60 mL/min/1.73 m^2). Population PK analysis indicated no impact of renal impairment on the exposure (Cmax and AUC) of QFITLIA in patients with mild renal impairment.

Drug Interaction Studies

Clinical Studies

No clinical drug-drug interaction studies have been conducted to evaluate the potential of QFITLIA to interact with other co-administered drugs which are either substrates, inhibitors or inducers of CYP isozymes, or are substrates or inhibitors of drug transporters.

In Vitro Studies

Results from in vitro studies evaluating the potential of co-administered drugs to increase the PK exposure of QFITLIA, and the potential of QFITLIA to increase the PK exposure of co-administered drugs, indicate that CYP- or transporter-mediated interactions between QFITLIA and co-administered drugs are unlikely at clinically relevant concentrations.

12.6 Immunogenicity

The observed incidence of anti-drug antibodies (ADA) is highly dependent on the sensitivity and specificity of the assay. Differences in assay methods preclude meaningful comparisons of the incidence of ADA in the studies described below with the incidence of ADA in other studies, including those of QFITLIA or of other fitusiran products.

During QFITLIA treatment (up to 250 weeks) in four studies, 10 out of 290 adults with hemophilia (3.4%) developed ADAs. All patients had low ADA titers, and the majority of patients had transient ADAs. There was no identified clinically significant effect of ADAs on PK, PD, safety, or effectiveness of QFITLIA.

13 NONCLINICAL TOXICOLOGY

13.1 Carcinogenesis, Mutagenesis, Impairment of Fertility

In a 2-year carcinogenicity study in Sprague Dawley rats, fitusiran was not carcinogenic up to the highest dose tested following subcutaneous administration at doses of 0.03, 0.1 or 0.3 mg/kg/week in males and 0.1, 0.3, or 1 mg/kg/week in females. All doses in males and females were below the maximum recommended human dose (MRHD) of 50 mg per month based on body surface area (BSA) comparisons due to the sensitivity of wild type animals to the pharmacological effects of fitusiran. Fitusiran was not carcinogenic in Tg-rasH2 mice following subcutaneous administration at doses of 0.05, 0.15, or 0.5 mg/kg/week in males and 0.025, 0.08, or 0.25 mg/kg/week in females for 26 weeks.

Fitusiran was not mutagenic or clastogenic in a battery of genetic toxicity studies (i.e., in vitro bacterial reverse mutation assay, in vitro chromosomal aberration assay in human peripheral blood lymphocytes; in vivo bone marrow micronucleus test in rats).

In a chronic repeat dose toxicology study in Sprague Dawley rats, fitusiran-treated males received subcutaneous doses of 0.25, 0.5, or 1 mg/kg/week for 16 weeks then were cohabitated with fitusiran-naïve females. No adverse effects on male fertility endpoints were observed. All doses used in males were below the MRHD based on BSA comparisons due to the sensitivity of wild type animals to the pharmacological effects of fitusiran.

14 CLINICAL STUDIES

The efficacy and safety of QFITLIA in adult and pediatric patients aged 12 years and older with hemophilia A or B with or without inhibitors were established in two clinical studies:

- Hemophilia A or B with Inhibitory Antibodies: ATLAS-INH (NCT03417102)
- Hemophilia A or B without Inhibitory Antibodies: ATLAS-A/B (NCT03417245)

Patients in the above parent studies rolled over into the long-term extension study ATLAS-OLE (NCT03754790).

The clinical studies ATLAS-INH and ATLAS-A/B tested an 80 mg monthly fixed dose of QFITLIA. Because of thrombotic events with this dose, the QFITLIA AT-DR targeting AT activity of 15–35% was implemented in ATLAS-OLE. The AT-DR was initiated when studies ATLAS-INH and ATLAS-A/B were nearly completed, therefore, the efficacy of QFITLIA AT-DR treatment was assessed by comparing the QFITLIA AT-DR treatment data from the long-term extension study ATLAS-OLE to the control data from studies ATLAS-INH and ATLAS-A/B. The efficacy analyses were conducted according to the intent to treat (ITT) principle preserving the randomization in the parent studies.

ATLAS-INH

ATLAS-INH was a randomized, multicenter, open-label clinical study in 57 adult and pediatric males (aged ≥12 years) with hemophilia A or B with inhibitory antibodies to factor VIII (FVIII) or factor IX (FIX), who previously received on-demand (episodic) treatment with BPAs for bleeding. Eligible patients were randomized in a 2:1 ratio to receive QFITLIA prophylaxis at a fixed dose 80 mg SC monthly (N=38) or BPA on-demand for treatment of breakthrough bleeding episodes (N=19) for 9 months. The 80 mg dose of QFITLIA is not approved because of an increased risk of serious thrombotic events, gallbladder events (including the need for cholecystectomy) and hepatotoxicity [see Boxed Warning and Warnings and Precautions (5.1, 5.2, 5.3)].

Of the 57 enrolled patients all had inhibitors; 45 patients had Hemophilia A and 12 had Hemophilia B. All patients in the study were male. The mean age of patients was 28.4 years, and 10 (17.5%) patients were 12–17 years of age. A total of 68.4% of patients were Asian, 28.1% were White, 1.8% were other, and 1.8% were multiple races; 5.3% patients identified as Hispanic or Latino and 94.7% identified as not Hispanic or Latino. Generally, the demographic and patient characteristics at baseline were comparable between the patients with hemophilia A and B.

ATLAS A/B

ATLAS A/B was a randomized, multicenter, open-label clinical study in 120 adult and pediatric males (aged ≥12 years) with hemophilia A or B without inhibitory antibodies to FVIII or FIX, who previously received on-demand (episodic) treatment with CFC for bleeding. Eligible patients were randomized in a 2:1 ratio to receive QFITLIA prophylaxis at a fixed dose of 80 mg SC monthly (N=80) or CFCs on-demand to treat breakthrough bleeding episodes (N=40) for 9 months. The 80 mg dose of QFITLIA is not approved because of an increased risk of serious thrombotic events, gallbladder events (including the need for cholecystectomy) and hepatotoxicity [see Boxed Warning and Warnings and Precautions (5.1, 5.2, 5.3)].

Of the 120 enrolled patients none had inhibitors; 93 patients had Hemophilia A and 27 had Hemophilia B. All patients in the study were male. The mean age of patients was 33.8 years, and 14 (11.7%) patients were 12–17 years of age. A total of 59.2% of patients were Asian, 37.5% were White, 1.7% were Black or African American, and 1.7% were multiple races; 3.3% of patients identified as Hispanic or Latino, 90.8% identified as not Hispanic or Latino, and 5.8% had ethnicity information unreported. Generally, the demographic and patient characteristics at baseline were comparable between the patients with hemophilia A and B.

ATLAS-OLE

A total of 227 patients rolled over from two clinical studies (ATLAS-INH and ATLAS-A/B) and ATLAS-PPX, a crossover study in patients previously on CFC or BPA prophylaxis, and were treated with QFITLIA in ATLAS-OLE. This multicenter open-label extension study evaluated the long-term safety and efficacy of QFITLIA in adult and pediatric males aged ≥12 years with hemophilia A or B, with or without inhibitory antibodies to FVIII or FIX. Eligible patients initially received QFITLIA 80 mg SC once monthly. The study was amended to evaluate the efficacy and safety of the AT-DR. A total of 213 patients were subsequently transitioned to AT-DR targeting AT activity of 15–35%.

In the AT-DR, the QFITLIA starting dose was 50 mg every two months, and dosing was individually adjusted based on AT activity level using the INNOVANCE Antithrombin assay. The dose could be increased to 50 mg every month or 80 mg every month or decreased to 20 mg every two months or 20 mg every month. QFITLIA was discontinued if AT activity was <15% at the lowest dose. No patients required escalation to 80 mg every month to achieve the target AT range. The dose required to maintain AT activity 15–35% in patients who initiated dosing on 50 mg every two months was: 50 mg every two months (35.8% of patients), 50 mg every month (15.7% of patients), 20 mg every two months (30.9% of patients), or 20 mg every month (2.9% of patients). A total of 14.7% of patients discontinued QFITLIA due to more than one AT activity <15%.

Patients with known co-existing coagulation disorders other than hemophilia A or B, increased risk of thrombosis as assessed by history of arterial or venous thromboembolism, significant valvular disease or atrial fibrillation, or co-existing thrombophilic disorder (e.g., Factor V Leiden mutation), AT activity <60% at screening, platelet count ≤100,000/μL, eGFR ≤45 mL/min (using the MDRD), or clinically significant liver disease were not eligible for enrollment.

The efficacy of QFITLIA AT-DR in ATLAS-OLE was evaluated for a duration of 7 months (primary efficacy period) following a 6-month dose adjustment period. The median observed annualized bleeding rate (IQR) for treated bleeds was 3.7 (0.0; 7.5) overall, 1.9 (0.0; 5.6) in inhibitor patients and 3.8 (0.0; 11.2) in non-inhibitor patients.

QFITLIA Prophylaxis Compared to On-Demand BPA or CFC

The efficacy results of QFITLIA prophylaxis using AT-DR in ATLAS-OLE compared to on-demand BPA or CFC control data from studies ATLAS-INH and ATLAS-A/B with respect to rate of treated bleeds, treated spontaneous bleeds, and treated joint bleeds are shown in Table 5 (patients with inhibitors) and Table 6 (patients without inhibitors) below.

Table 5: Annualized Bleed Rate for Treated Bleeds with QFITLIA Prophylaxis versus On-Demand BPA in Patients ≥12 Years of Age with Inhibitors
Endpoint | QFITLIA AT-DR (N=38) | On-Demand BPA (N=19)
All Treated Bleeds
ABR (95% CI) [Based on negative binomial regression model.] | 5.1 (2.8, 9.5) | 19.1 (11.8, 31.0)
% reduction p-value | 73% p=0.0006
Treated Spontaneous Bleeds
ABR (95% CI) | 3.1 (1.8, 5.4) | 17.1 (9.9, 29.6)
% reduction p-value | 82% <0.0001
Treated Joint Bleeds
ABR (95% CI) | 4.0 (2.5, 6.2) | 14.4 (9.0, 23.1)
% reduction p-value | 73% p=0.0001
ABR = annualized bleed rate; AT-DR = AT-Dosing Regimen; BPA = bypassing agents; CI = confidence interval.

Table 6: Annualized Bleed Rate for Treated Bleeds with QFITLIA Prophylaxis versus On-Demand CFC in Patients ≥12 Years of Age without Inhibitors
Endpoint | QFITLIA AT-DR (N=80) | On-Demand CFC (N=40)
All Treated Bleeds
ABR (95% CI) [Based on negative binomial regression model.] | 9.0 (5.6, 14.5) | 31.4 (20.5, 48.2)
% reduction p-value | 71% p<0.0001
Treated Spontaneous Bleeds
ABR (95% CI) | 5.4 (3.7, 8.0) | 21.0 (14.0, 31.6)
% reduction p-value | 74% p<0.0001
Treated Joint Bleeds
ABR (95% CI) | 6.2 (4.2, 9.2) | 21.6 (14.6, 31.9)
% reduction p-value | 71% p<0.0001
ABR = annualized bleed rate; AT-DR = AT-Dosing Regimen; CFC = clotting factor concentrate; CI = confidence interval.

16 HOW SUPPLIED/STORAGE AND HANDLING

16.1 How Supplied

QFITLIA (fitusiran) is a clear, colorless to pale yellow solution supplied in a single-dose prefilled pen or a single-dose vial. Each prefilled pen is designed to deliver 50 mg of QFITLIA in 0.5 mL (NDC 58468-0348-1). Each vial is designed to deliver 20 mg of QFITLIA in 0.2 mL (NDC 58468-0347-1).

QFITLIA is available in cartons containing 1 prefilled pen or 1 vial.

16.2 Storage and Handling

50 mg Prefilled Pen

- Store refrigerated at 2°C to 8°C (36°F to 46°F) in the original carton to protect from light.
- QFITLIA may be stored at room temperature between 15°C to 30°C (59°F to 86°F) for a single period of up to 3 months within the expiration date printed on the label. Discard no later than 3 months after removal from the refrigerator or at the expiration date, whichever comes first. After storage at room temperature, do not return the product to the refrigerator.

20 mg Vial

- Store QFITLIA either in the refrigerator at 2°C to 8°C (36°F to 46°F) or at room temperature between 15°C to 30°C (59°F to 86°F), in the original carton to protect from light. After storage at room temperature, do not return the product to the refrigerator.

Do not shake QFITLIA at any time. Do not heat QFITLIA. Do not freeze. Do not put into direct sunlight.

17 PATIENT COUNSELING INFORMATION

- Advise the patient to read the FDA-approved patient labeling (Medication Guide and Instructions for Use).

Use of BPAs or CFCs

Advise the patient and/or caregiver to discontinue prophylactic use of BPA or CFC no later than 7 days after starting QFITLIA to reduce the risk of thrombotic events. Discuss the appropriate dosing and frequency of BPA or CFC for breakthrough bleed management with the patient and/or caregiver prior to starting QFITLIA prophylaxis [see Dosage and Administration (2.3)].

Thrombotic Events

Advise the patient and/or caregiver of the risk of thrombotic events while receiving QFITLIA. Inform the patient and/or caregiver of the need for periodic measurements of AT activity that may result in changes to the QFITLIA dose and/or frequency of administration to reduce the risk for thrombosis. Educate patients on the signs and symptoms of thrombotic events and to seek immediate medical attention if new symptoms of thrombotic events occur [see Warnings and Precautions (5.1)].

Acute and Recurrent Gallbladder Disease

Inform the patient and/or caregiver of the risk of acute and recurrent gallbladder disease while receiving QFITLIA. Educate patients on the signs and symptoms of gallbladder disease and to seek medical attention if new symptoms of gallbladder disease occur [see Warnings and Precautions (5.2)].

Hepatotoxicity

Inform the patient and/or caregiver of the risk of hepatotoxicity and that blood tests to monitor for this risk will be obtained before starting QFITLIA and periodically during treatment. Inform patients to seek medical attention if symptoms of hepatotoxicity occur [see Warnings and Precautions (5.3)].

Administration Instructions

Provide training to the patient and/or caregiver on proper subcutaneous injection technique, including aseptic technique, and the preparation and administration of QFITLIA prior to use [see Dosage and Administration (2.4)].

Manufactured by:
Genzyme Corporation
Cambridge, MA 02141
A SANOFI COMPANY
© 2025 GENZYME CORPORATION. All rights reserved.

For patent information: https://www.sanofi.us/en/products-and-resources/patents

QFITLIA is a registered trademark of GENZYME CORPORATION

MEDICATION GUIDE
QFITLIA® (kew fit lee ah)
(fitusiran)
injection, for subcutaneous use

What is the most important information I should know about QFITLIA?

QFITLIA helps your blood form clots. Do not stop using QFITLIA without talking to your healthcare provider. If you miss doses or stop using QFITLIA, you may no longer be protected against bleeding.

Use of a clotting factor concentrate (CFC) or bypassing agent (BPA) to help protect against bleeding must be stopped within 7 days after your first dose of QFITLIA.

Your healthcare provider may prescribe on demand CFC (factor VIII or factor IX products) or BPA if you bleed during treatment with QFITLIA. Carefully follow your healthcare provider's instructions regarding when to use on-demand treatment with CFC or BPA, including the prescribed dose and timing of the CFC or BPA.

QFITLIA can cause serious side effects, including:

- Abnormal blood clotting (thrombotic events). Serious blood clots have happened in people treated with QFITLIA. QFITLIA can cause blood clots to form in blood vessels in your arms, legs, lungs, heart, brain, eyes, or head. Your risk of blood clots is greater if your antithrombin (AT) blood level is persistently less than 15% or if you have certain other conditions. Get medical help right away if you get any of these signs or symptoms of blood clots during or after treatment with QFITLIA:

- swelling, pain or redness in arms or legs
- coughing up blood
- shortness of breath
- severe chest pain or tightness of the chest
- fast heart rate
- feeling faint or passing out

- severe or persistent headache
- difficulty speaking or understanding language
- feel confused
- numbness or weakness in your face, arms or legs
- sudden loss or changes in your vision, eye pain or swelling

- Gallbladder disease. QFITLIA can cause gallstones (cholelithiasis) and inflammation of your gallbladder (cholecystitis), which might require surgery to remove your gallbladder. Tell your healthcare provider right away if you develop stomach (abdomen) pain, indigestion, nausea or vomiting. Your healthcare provider may temporarily or permanently stop your treatment with QFITLIA if you develop any of these symptoms.
- Liver problems. QFITLIA can cause an increase in your blood liver enzymes. Your healthcare provider will do blood tests to check your liver function before and during treatment with QFITLIA.
- See "What are the possible side effects of QFITLIA?" for more information about side effects.

What is QFITLIA?
QFITLIA is a prescription medicine used for routine prophylaxis to prevent or reduce the frequency of bleeding episodes in adults and children 12 years and older with hemophilia A or B with or without factor VIII or IX inhibitors.
It is not known if QFITLIA is safe and effective in children younger than 12 years of age.

Before receiving QFITLIA, tell your healthcare provider about all of your medical conditions, including if you:

- have liver problems
- have a history of gallbladder disease
- are pregnant or plan to become pregnant. It is not known if QFITLIA may harm your unborn baby.
  Females who are able to become pregnant: Hormonal birth control (contraception) may increase your risk of blood clots if used during treatment with QFITLIA. If you use hormonal birth control (contraception), talk to your healthcare provider about effective forms of non-hormonal birth control (contraception) options you can use before starting and during treatment with QFITLIA.
- are breastfeeding or plan to breastfeed. It is not known if QFITLIA passes into your breast milk.

Tell your healthcare provider about all the medicines you take, including prescription and over-the-counter medicines, vitamins, and herbal supplements. Keep a list of them to show your healthcare provider and pharmacist when you get a new medicine.

How should I use QFITLIA?
See the detailed "Instructions for Use" that comes with your QFITLIA for information on how to prepare and inject a dose of QFITLIA, and how to properly throw away (dispose of) the used prefilled pen, vial, needle and syringe.

- Use QFITLIA exactly as prescribed by your healthcare provider.
- Your healthcare provider may change your dose or how often you inject QFITLIA based on your AT blood level to help reduce your chance of abnormal blood clots. Your healthcare provider will check your AT blood level:
  - before starting QFITLIA and at month 1, 3, 5 and 6 during QFITLIA treatment.
  - after any change in your dose of QFITLIA.
  - at yearly routine visits after your healthcare provider determines your target dose.
- It is recommended that QFITLIA be given by or under the supervision of an adult in children 12 to 17 years of age.
- QFITLIA is given as an injection under your skin (subcutaneous) by you or a caregiver.
- Your healthcare provider should show you or your caregiver how to prepare, measure, and inject your dose of QFITLIA before you inject yourself for the first time.
- Do not attempt to inject yourself or another person unless you have been taught how to do so by a healthcare provider.
- After your first dose of QFITLIA, your healthcare provider will let you know when to take your next dose and how much QFITLIA to inject.
- If you miss a dose of QFITLIA on your scheduled day, you should give the dose as soon as possible. After that, resume your dosing schedule either 1 time every month or 1 time every two months from the last dose, as instructed by your healthcare provider.

What are the possible side effects of QFITLIA?

- See "What is the most important information I should know about QFITLIA?"

The most common side effects of QFITLIA include:

- viral infection
- common cold symptoms
- bacterial infection

These are not all of the possible side effects of QFITLIA.
Call your doctor for medical advice about side effects. You may report side effects to the FDA at 1-800-FDA-1088.

How should I store QFITLIA?

- 50 mg Prefilled Pen
  - Store QFITLIA prefilled pen in the refrigerator between 36°F to 46°F (2°C to 8°C) in the original carton to protect from light.
  - QFITLIA prefilled pen may be stored at room temperature between 59°F to 86°F (15°C to 30°C) for a single period of up to 3 months within the expiration date printed on the label.
  - Throw away (dispose of) the QFITLIA prefilled pen after 3 months at room temperature or at the expiration date, whichever comes first.
  - Do not return QFITLIA prefilled pen to the refrigerator after storing at room temperature.
- 20 mg Vial
  - Store QFITLIA vial in the refrigerator between 36°F to 46°F (2°C to 8°C) or at room temperature between 59°F to 86°F (15°C to 30°C) in the original carton to protect from light.
  - Do not return QFITLIA vial to the refrigerator after storing at room temperature.
- Do not shake the QFITLIA vial or prefilled pen at any time.
- Do not heat the QFITLIA vial or prefilled pen.
- Do not freeze the QFITLIA vial or prefilled pen.
- Do not put the QFITLIA vial or prefilled pen into direct sunlight.
- Throw away (dispose of) any unused QFITLIA.

Keep QFITLIA and all medicines out of the reach of children.

General information about the safe and effective use of QFITLIA.
Medicines are sometimes prescribed for purposes other than those listed in a Medication Guide. Do not use QFITLIA for a condition for which it was not prescribed. Do not give QFITLIA to other people even if they have the same symptoms you have. It may harm them. You can ask your healthcare provider or pharmacist for information about QFITLIA that is written for health professionals.

What are the ingredients in QFITLIA?
Active ingredient: fitusiran
Inactive ingredients: dibasic sodium phosphate, monobasic sodium phosphate, sodium chloride, and Water for Injection, USP. Phosphoric acid (concentrated) and sodium hydroxide may be added to adjust pH to 7.
Manufactured by: Genzyme Corporation, Cambridge, MA 02141. A SANOFI COMPANY.
For patent information: https://www.sanofi.us/en/products-and-resources/patents
©2025 Genzyme Corporation. All rights reserved.
For more information, go to www.QFITLIA.com or call 1-800-745-4447.

This Medication Guide has been approved by the U.S. Food and Drug Administration.

Issued: September 2025

INSTRUCTIONS FOR USE

QFITLIA® (kew fit lee ah)
(fitusiran)
injection, for subcutaneous use
Single-Dose Prefilled Pen (50 mg/0.5 mL)

This Instructions for Use contains information on how to inject QFITLIA.

Read this Instructions for Use before using the QFITLIA Prefilled Pen. Do not inject yourself or someone else until you have been shown how to inject QFITLIA Prefilled Pen. Your healthcare provider can show you or your caregiver how to prepare and inject a dose of QFITLIA before you try to do it yourself for the first time. Keep this Instructions for Use. Call your healthcare provider if you have any questions.

QFITLIA Prefilled Pen is only for use in adults and children 12 years of age and older. It is recommended that QFITLIA Prefilled Pen be given by adults or under adult supervision to children 12 to 17 years of age.

This QFITLIA Prefilled Pen is a single-dose device. It contains 50 mg of QFITLIA for injection under the skin (subcutaneous injection).

The parts of the QFITLIA Prefilled Pen are shown below:

Important information to know before injecting QFITLIA

- Read all of the instructions carefully before using the QFITLIA Prefilled Pen.
- Ask your healthcare provider how often you will need to inject the medicine.
- Throw away (dispose of) the used QFITLIA Prefilled Pen right away after use.
- Do not re-use a QFITLIA Prefilled Pen.
- QFITLIA Prefilled Pen is for subcutaneous use only. Do not inject QFITLIA Prefilled Pen into a vein.

Storing QFITLIA Prefilled Pen

- Store QFITLIA Prefilled Pen in the refrigerator between 36°F to 46°F (2°C to 8°C) in the original carton to protect from light.
- QFITLIA Prefilled Pen may be stored at room temperature between 59°F to 86°F (15°C to 30°C) for a single period of up to 3 months within the expiration date printed on the label.
- Do not return QFITLIA Prefilled Pen to the refrigerator after storing at room temperature.
- Do not shake the QFITLIA Prefilled Pen at any time.
- Do not heat the QFITLIA Prefilled Pen.
- Do not freeze the QFITLIA Prefilled Pen.
- Do not put the QFITLIA Prefilled Pen into direct sunlight.
- Keep QFITLIA Prefilled Pen and all medicines out of the reach of children.

A. Get ready to inject

A1) Gather supplies

Find a clean, flat work surface. Make sure you have the following supplies:

A2) Check the QFITLIA Prefilled Pen

- Note: The plunger stopper in the middle of the Window is normal.
- Do not use the QFITLIA Prefilled Pen if it has been dropped or damaged.
- Do not use the QFITLIA Prefilled Pen if the Blue Cap is missing or not securely attached.
- Do not use the QFITLIA Prefilled Pen if the Window is yellow before use. A yellow Window means the QFITLIA Prefilled Pen has been used.

A3) Look at the label

- Check the label to be sure that you have the correct prescribed medicine and dose.

- Check the expiration date.
- Do not use the QFITLIA Prefilled Pen if the expiration date has passed.

A4) Check the medicine

- Look at the medicine through the Window, it should be clear and colorless to pale yellow.
- Note: You may see air bubbles, this is normal.
- Do not use the QFITLIA Prefilled Pen if the liquid is discolored or cloudy, or if it contains visible flakes or particles.

A5) If QFITLIA Prefilled Pen was stored in the refrigerator, warm up for 30 minutes.

- Lay the QFITLIA Prefilled Pen on a clean, flat surface and let it warm up at room temperature between 59°F to 86°F (15°C to 30°C) for at least 30 minutes.
- Do not heat the QFITLIA Prefilled Pen or put into direct sunlight.

B. Choose and prepare your injection site

B1) Wash your hands well with soap and water

B2) Choose an injection site

- Thigh
- Stomach except for the 2 inches (5 cm) around your belly button (navel).
- A caregiver can also inject in the outer area of your upper arm.
- Do not inject into skin that is tender, damaged, has bruises or scars, or into areas with visible veins.
- For subcutaneous use only. Do not inject into a vein.
- Do not inject through clothes.

B3) Prepare the injection site

- Clean the injection site with an alcohol wipe.
- Let the skin dry before injecting.
- Do not touch the injection site again or blow on it before the injection.

C. Give the injection

C1) Remove Blue Cap

- Remove the Blue Cap by pulling it straight off as shown. Do not twist the Blue Cap off.
- Do not remove the Blue Cap until you are ready to inject.
- Do not touch the Orange Needle Cover with your fingers. The Needle is inside.
- Do not put the Blue Cap back on the QFITLIA Prefilled Pen after you have removed it.
- Note: You may see a droplet on the needle tip. This is normal.

C2) Place QFITLIA Prefilled Pen on injection site

- Hold the QFITLIA Prefilled Pen as shown so you can see the Window.
- Place the Orange Needle Cover on the skin at a 90-degree angle.

C3) Press down firmly → Watch Window turn fully yellow

Press down and hold the QFITLIA Prefilled Pen firmly against the skin until you cannot see the Orange Needle Cover.

- There will be a "click" when the injection starts, and
- The Window will start to turn yellow.

Keep pressing the QFITLIA Prefilled Pen against the skin and watch the Window.

- The Window will turn completely yellow, and
- You may hear a 2nd "click." The injection is complete.

C4) Remove

- After you have completed your injection pull straight up to remove QFITLIA Prefilled Pen from the skin. The Orange Needle Cover will cover the needle.
- If you see any blood at the site, lightly dab a cotton ball or gauze pad.
- Do not rub the skin after the injection.
- If the Window does not turn completely yellow, or if it looks like you may not have received a full dose, call your healthcare provider right away.
- Do not give a second dose without speaking to your healthcare provider.

D. Throw away (dispose of) used QFITLIA Prefilled Pen

- Do not put the Blue Cap back on.

Keep your sharps disposal container out of the reach of children.

How to dispose of (throw away) QFITLIA Prefilled Pen

- Put your used QFITLIA Prefilled Pen and Blue Cap in an FDA-cleared sharps disposal container right away after use.
- Do not dispose of (throw away) QFITLIA Prefilled Pen and Blue Cap in your household trash.
- If you do not have an FDA-cleared sharps disposal container, you may use a household container that is:
  - made of a heavy-duty plastic,
  - can be closed with a tight-fitting, puncture-resistant lid, without sharps being able to come out,
  - upright and stable during use,
  - leak-resistant, and
  - properly labeled to warn of hazardous waste inside the container.
- When your sharps disposal container is almost full, you will need to follow your community guidelines for the right way to dispose of your sharps disposal container. There may be state or local laws about how you should throw away used QFITLIA Prefilled Pens.
- For more information about safe sharps disposal, and for specific information about sharps disposal in the state that you live in, go to the FDA's website at: http://www.fda.gov/safesharpsdisposal
- Do not dispose of your used sharps disposal container in your household trash unless your community guidelines permit this.
- Do not recycle your used sharps disposal container.

Manufactured by:
Genzyme Corporation
Cambridge, MA 02141
A SANOFI COMPANY

QFITLIA is a registered trademark of GENZYME CORPORATION
© 2025 GENZYME CORPORATION. All rights reserved.

For patent information: https://www.sanofi.us/en/products-and-resources/patents

For more information go to www.QFITLIA.com or call 1-800-745-4447.

This Instructions for Use has been approved by the US Food and Drug Administration.
Issued: September 2025

INSTRUCTIONS FOR USE

QFITLIA® (kew fit lee ah)
(fitusiran)
injection, for subcutaneous use
Single-Dose Vial (20 mg/0.2 mL)

This Instructions for Use contains information on how to inject QFITLIA from a vial.

Read this Instructions for Use before using QFITLIA. Do not inject yourself or someone else until you have been shown how to inject QFITLIA from a vial. Your healthcare provider can show you or your caregiver how to prepare and inject a dose of QFITLIA from a vial before you do it yourself for the first time. Keep this Instructions for Use. Call your healthcare provider if you have any questions.

QFITLIA is only for use in adults and children 12 years of age and older. In children 12 to 17 years of age it is recommended that QFITLIA be given by or under the supervision of an adult.

This QFITLIA vial is for single-use only. It contains 20 mg of QFITLIA for injection under the skin (subcutaneous injection).

Important information to know before injecting QFITLIA

- Read all of the instructions carefully before using QFITLIA.
- Ask your healthcare provider how often you will need to inject the medicine.
- Check your prescription label to make sure you draw up the correct medicine dose prescribed by your healthcare provider.
- Throw away (dispose of) the used vial, syringe and needle right away after use.
- Only use the vial one time. After you inject your dose, throw away (dispose of) any unused QFITLIA left in the vial. Do not save any unused QFITLIA in the vial for later use.
- QFITLIA is for subcutaneous use only. Do not inject QFITLIA into a vein.

Storing QFITLIA vial

- Store QFITLIA vial either in the refrigerator between 36°F to 46°F (2°C to 8°C) or at room temperature between 59°F to 86°F (15°C to 30°C) in the original carton to protect from light.
- Do not return QFITLIA vial to the refrigerator after storing at room temperature.
- Do not shake the QFITLIA vial at any time.
- Do not heat the QFITLIA vial.
- Do not freeze the QFITLIA vial.
- Do not put the QFITLIA vial into direct sunlight.
- Keep QFITLIA vial and all medicines out of the reach of children.

A. Get ready to inject

A1) Gather the supplies.

Find a clean, flat work surface. Make sure you have the following supplies:

A2) Check the vial.

- Do not use the QFITLIA vial if it has been dropped or damaged.
- Check the label on the vial to be sure that you have the correct prescribed medicine and dose.
- Check expiration date (EXP:).
- Do not use QFITLIA if the expiration date on the vial has passed.

A3) Check the medicine.

- Look at the medicine in the vial to make sure it is clear and colorless to pale yellow.
- Do not use QFITLIA if the liquid in the vial is discolored or cloudy, or if it contains visible flakes or particles.

A4) If the QFITLIA vial was stored in the refrigerator, warm up for 30 minutes.

- Set the QFITLIA vial on a clean, flat surface and let it warm up at room temperature between 59°F to 86°F (15°C to 30°C) for at least 30 minutes.
- Do not heat the QFITLIA vial or put in direct sunlight.

A5) Wash your hands well with soap and water.

A6) Remove the protective cap from the QFITLIA vial.
Do not remove the stopper.

A7) Wipe the rubber stopper of the vial with an alcohol wipe and allow it to dry.

B. Choose and prepare the injection site

B1) Choose the injection site.

- Thigh
- Stomach except for the 2 inches (5 cm) around your belly button (navel).
- A caregiver can also inject in the outer area of your upper arm.
- Do not inject into skin that is tender, damaged, has bruises or scars, or into areas with visible veins.
- Do not inject into a vein. For subcutaneous use only.
- Do not inject through clothes.

B2) Prepare the injection site.

- Clean the injection site with an alcohol wipe.
- Let the skin dry before injecting.
- Do not touch the injection site again or blow on it before the injection.

C. Prepare the injection
Contact your healthcare provider if you have any questions about preparing your dose.

C1) Attach the needle to the syringe and remove the needle cap.

- Attach the needle to the syringe.
- Hold the syringe body and pull the needle cap straight off the syringe.
- Do not touch the needle.
- Do not recap the needle.

C2) Withdraw the solution.

Withdraw slightly more than your prescribed dose into the syringe.

- Push the needle through the center of the rubber vial stopper.
- Leave the needle in the vial and turn both the syringe and vial upside down (vial on top).
- Hold the syringe and vial firmly in one hand. Make sure the tip of the needle is in the QFITLIA solution.
- With your other hand, pull back on the plunger rod to withdraw slightly more than your prescribed dose into the syringe.
  - Withdraw slightly more than 0.2 mL for a 20 mg dose.
  - Withdraw slightly more than 0.1 mL for a 10 mg dose.

C3) Check for air bubbles.

- Keep the needle in the vial and make sure both syringe and vial are upside down (vial on top).
- If air bubbles are in the syringe, hold the syringe straight up and tap the side of the syringe until the bubbles float to the top.
- Push the plunger rod up to push the bubbles out of the syringe.

C4) Adjust plunger to your prescribed dose.

- Push the plunger rod to push solution back into the vial until you have the prescribed dose in the syringe.
  - Push plunger rod to 0.2 mL for a 20 mg dose.
  - Push plunger rod to 0.1 mL for a 10 mg dose.
- If the medicine in the syringe is less than your prescribed dose, repeat steps C2, C3 and C4 until you have your correct dose.
- Remove the needle from the vial. Do not let the needle touch anything.

D. Inject QFITLIA

D1) Pinch a fold of skin and insert the needle.

Gently pinch a fold of skin at the cleaned injection site. Insert the needle into the skin fold at a 45° to 90° angle.

D2) Inject QFITLIA.

Relax the skin pinch. Slowly push the plunger rod all the way to the bottom of the syringe body and inject all of the QFITLIA solution.

D3) Gently pull out the needle and syringe from the injection site.

- Do not recap the used needle to avoid a needle-stick injury.
- Do not rub the skin after the injection.
- If you see any blood at the site, lightly dab it with a cotton ball or gauze pad. If your injection site becomes red or sore, call your healthcare provider right away.

E. Throw away (dispose of) used vial, needle and syringe

E1) Throw away (dispose of) your used vial, needle and syringe in an FDA-cleared sharps disposal container right away after use.

Do not re-use the vial, needle, or syringe.

Keep your sharps disposal container out of the reach of children.

If you do not have an FDA-cleared sharps disposal container, you may use a household container that is:

- made of a heavy-duty plastic,
- can be closed with a tightfitting, puncture-resistant lid, without sharps being able to come out,
- upright and stable during use,
- leak-resistant, and
- properly labeled to warn of hazardous waste inside the container.

When your sharps disposal container is almost full, you will need to follow your community guidelines for the right way to dispose of your sharps disposal container. There may be state or local laws about how you should throw away used QFITLIA needles and syringes.

For more information about safe sharps disposal, and for specific information about sharps disposal in the state that you live in, go to the FDA's website at: http://www.fda.gov/safesharpsdisposal

- Do not dispose of your used sharps disposal container in your household trash unless your community guidelines permit this.
- Do not recycle your used sharps disposal container.

Manufactured by:
Genzyme Corporation
Cambridge, MA 02141
A SANOFI COMPANY

QFITLIA is a registered trademark of GENZYME CORPORATION
© 2025 GENZYME CORPORATION. All rights reserved.

For patent information: https://www.sanofi.us/en/products-and-resources/patents

For more information go to www.QFITLIA.com or call 1-800-745-4447.

This Instructions for Use has been approved by the US Food and Drug Administration.
Issued: September 2025

PRINCIPAL DISPLAY PANEL - 0.5 mL Syringe Carton

NDC 58468-0348-1
Rx only

Qfitlia™
(fitusiran) injection
50 mg/0.5 mL

For Subcutaneous Use Only

Dispense the enclosed Medication Guide to each patient.

One 0.5 mL Single-Dose Prefilled Pen

sanofi

PRINCIPAL DISPLAY PANEL - 0.2 mL Vial Carton

NDC 58468-0347-1
Rx only

Qfitlia™
(fitusiran) injection
20 mg/0.2 mL

For Subcutaneous Use Only

Dispense the enclosed Medication
Guide to each patient.

One 0.2 mL Single-Dose Vial.
Discard Unused Portion.

sanofi